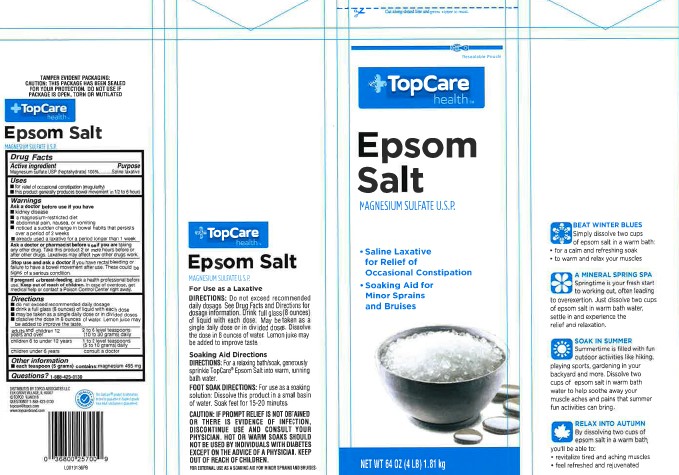 DRUG LABEL: Epsom Salt
NDC: 36800-602 | Form: GRANULE, FOR SOLUTION
Manufacturer: Topco Associates LLC
Category: otc | Type: HUMAN OTC DRUG LABEL
Date: 20260213

ACTIVE INGREDIENTS: MAGNESIUM SULFATE HEPTAHYDRATE 1 g/1 g

Top Care 602.02/602AA
Epsom Salt

Tamper Evident Statement

TAMPER EVIDENT PACKAGING:

CAUTION: THIS PACKAGE HAS BEEN SEALED FOR YOUR PROTECTION. DO NOT USE IF PACKAGE IS OPEN, TORN OR MUTILATED.

TopCare

health

Epsom Salt

MAGNESIUM SULFATE U.S.P.

Active ingredient

Magnesium sulfate USP (Heptahydrate) 100%

purpose

Saline laxative

Uses

- for relief of occasional constipation (irregularity)
- this product generally produces bowel movement in 1/2 to 6 hours

Warnings

for this product

Ask a Doctor before use if you have

- kidney disease
- a magnesium-restricted diet
- abdominal pain, nausea or vomiting
- noticed a sudden change in bowel habits that persists over a period of 2 weeks
- already used a laxative for a period longer than 1 week.

Ask a doctor or pharmacist before use if you are

taking any other drug. Take this product 2 or more hours before or after other drugs. Laxatives may affect how other drugs work.

Stop use and ask a doctor if

you have rectal bleeding or failure to have a bowel movement after use. These could be signs of a serious condition.

If pregnant or breast-feeding,

ask a health professional before use.

Keep out of reach of children.

In case of overdose, get medical help or contact a Poison Control Center right away.

directions

- do not exceed recommended daily dosage
- drink a full glass (8 ounces) of liquid with each dose
- may be taken as a single daily dose or in divided doses
- dissolve the dose in 8 ounces of water. Lemon juice may be added to improve the taste

adults and children 12 years and over - 2 to 6 level teaspoons (10 to 30 grams) daily

children 6 to under 12 years - 1 to 2 level teaspoons (5 to 10 grams) daily

children under 6 years - consult a doctor

inactive ingredients

None

Other information

- each teaspoon (5 grams) contains: magnesium 495 mg

Questions?

1-888-423-0139

ADVERSE REACTION

DISTRIBUTED BY TOPCO ASSOCIATES, LLC

ELK GROVE VILLAGE, IL 60007

©TOPCO

Questions? 1-888-423-0139

topcare@topco@com

www.topbrand.com

QUALITY GUARANTEED

Side Panel Claims

TopCare®

health

Epsom Salt

MAGNESIUM SULFATE U.S.P.

For Use as a Laxative

Directions:Do not exceed recommended daily dosage. See Drug Facts and Directions for dosage information. Drink full glass (8 ounces) of liquid with each dose. May be taken as a single dose or in divided doses. Dissolve the dose in 8 ounces of water. Lemon juice may be added to improve taste.

Soaking Aid Directions

Directions:For a relaxing bath/soak, generously sprinkle TopCare Epsom Salt into warm, running bath water.

Foot Soak Directions:For use as a soaking solution: Dissolve this product in a small basin of water. Soak feet for 15-20 minutes.

BEAT WINTER BLUES

Simply dissolve two cups of epsom salt in a warm bath:

- for a calm and refreshing soak
- to warm and relax your muscles

A MINERAL SPRING SPA

Springtime is your fresh start to working out, often leading to overexertion. Just dissolve two cups of epsom salt in warm bath water, settle in and experience the relief and relaxation.

SOAK IN SUMMER

Summertime is filles with fun outdoor activities like hiking, playing sports, gardening in your backyard and more. Dissolve two cups of epsom salt in warm bath water to help soothe away your muscle aches and pains that summer fun activities can bring.

RELAX INTO AUTUMN

By dissolving two cups of epsom salt in a warm bath, you'll be able to:

- revitalize tired and aching muscles
- feel refreshed and rejuvenated

principal display panel

Cut along dotted line and press zipper to reseal.

Resealable Pouch

TopCare health™

Epsom

Salt

MAGNESIUM SULFATE U.S.P.

- Saline Laxative for Relief of Occasional Constipation
- Soaking Aid for Minor Sprains and Bruises

NEW WT 64 OZ (4 LB) 1.81 kg